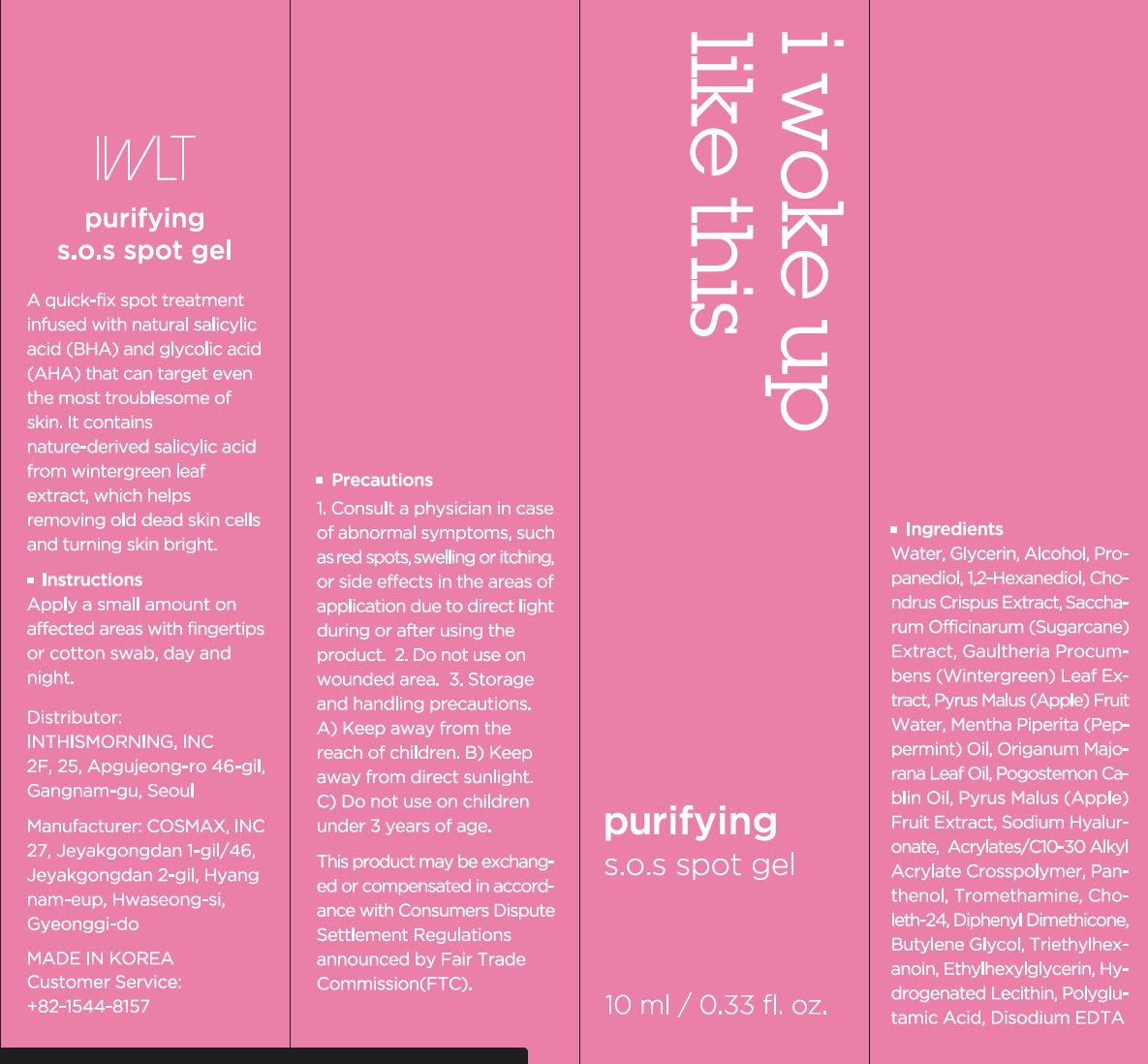 DRUG LABEL: Purifying S.O.S spotgel
NDC: 71217-0070 | Form: GEL
Manufacturer: inthismorning co ltd
Category: otc | Type: HUMAN OTC DRUG LABEL
Date: 20230204

ACTIVE INGREDIENTS: LIMONENE, (+)- 0.005016382 g/100 mL
INACTIVE INGREDIENTS: GLYCERIN; WATER

Drug Facts

ACTIVE INGREDIENT

limonene

INACTIVE INGREDIENT

Water
Glycerin
Alcohol
Propanediol
1,2-Hexanediol
Acrylates/C10-30 Alkyl Acrylate Crosspolymer
Panthenol
Tromethamine
Chondrus Crispus Extract
Choleth-24
Saccharum Officinarum (Sugarcane) Extract
Diphenyl Dimethicone
Butylene Glycol
Gaultheria Procumbens (Wintergreen) Leaf Extract
Triethylhexanoin
Pyrus Malus (Apple) Fruit Water
Ethylhexylglycerin
Hydrogenated Lecithin
Disodium EDTA
Origanum Majorana Leaf Oil
Mentha Piperita (Peppermint) Oil
Pogostemon Cablin Oil
Pyrus Malus (Apple) Fruit Extract
Polyglutamic Acid
Sodium Hyaluronate

PURPOSE

removing old dead skin cells and turning skin bright

keep out or reach of the children

INDICATIONS AND USAGE

apply a small amount on affected areas with fingertips or cotton swab, day and night

WARNINGS

This product is for exeternal use only. Do not use for internal use
Storage and handling precautions
If possible, avoid direct sunlight and store in cool and area of low humidity in order to maintain the quality of the product and avoid misuse
Avoid placing the product near fire and store out in reach of children

- consult a physician in case of abnormal symptoms, such as red spots, swelling or itching, or side effects in the areas of application due to direct light during or after using the product

- do not use on wounded area

DOSAGE AND ADMINISTRATION

for external use only